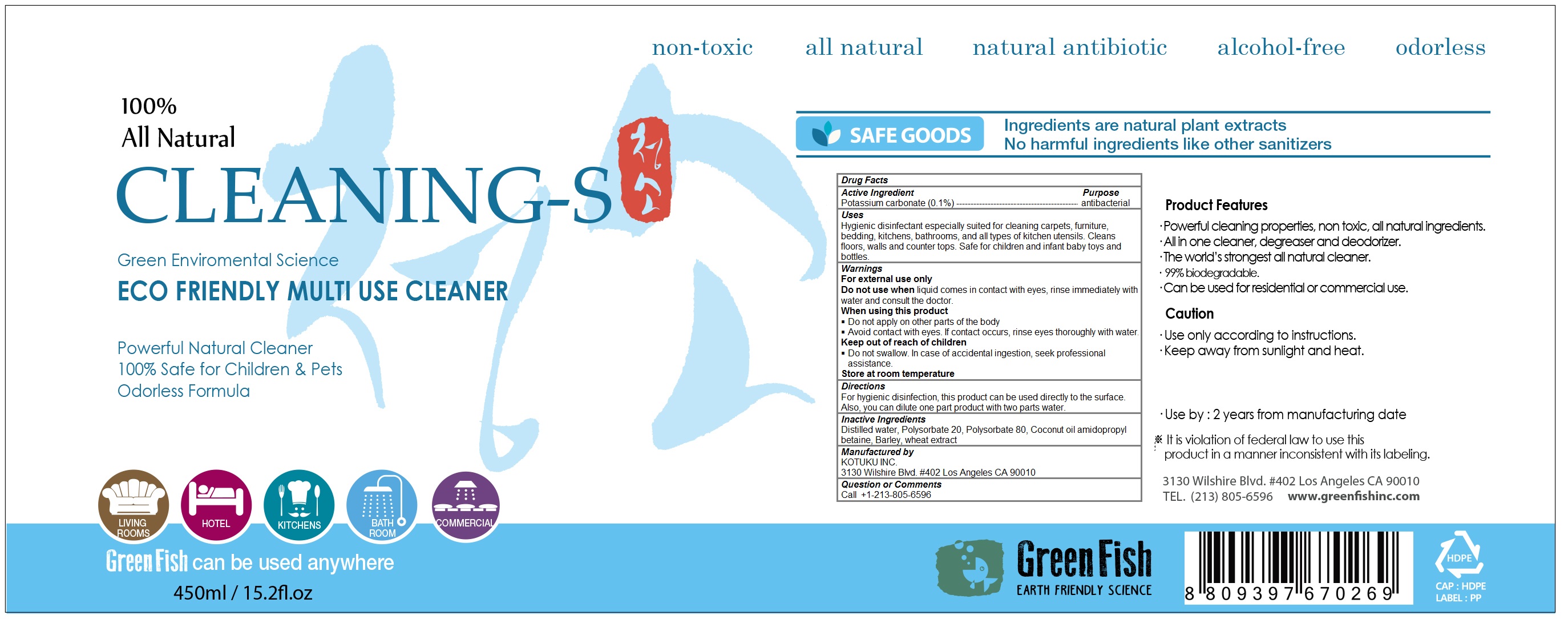 DRUG LABEL: Greenfish, Cleaning-S
NDC: 70610-101 | Form: LIQUID
Manufacturer: KOTUKU INC.
Category: otc | Type: HUMAN OTC DRUG LABEL
Date: 20160418

ACTIVE INGREDIENTS: POTASSIUM CARBONATE 0.001 1/450 mL
INACTIVE INGREDIENTS: CALCIUM HYDROXIDE; POLYSORBATE 20; POLYSORBATE 80; COCONUT OIL; WATER

Greenfish, Cleaning-S